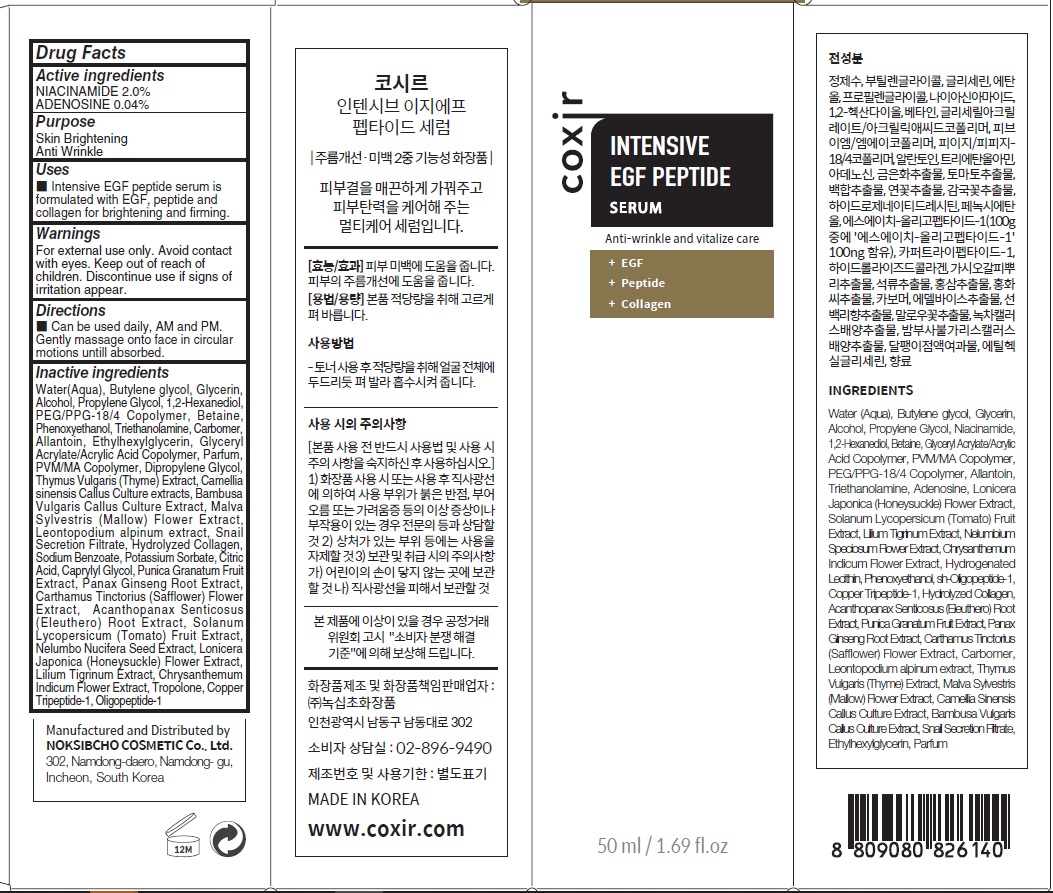 DRUG LABEL: COXIR INTENSIVE EGF PEPTIDE SERUM
NDC: 73590-0073 | Form: LIQUID
Manufacturer: NOKSIBCHO cosmetic Co., Ltd.
Category: otc | Type: HUMAN OTC DRUG LABEL
Date: 20210714

ACTIVE INGREDIENTS: NIACINAMIDE 1.0 g/50 mL; ADENOSINE 0.02 g/50 mL
INACTIVE INGREDIENTS: Water; Butylene Glycol; Glycerin

Drug Facts

ACTIVE INGREDIENTS

NIACINAMIDE 2.0%
ADENOSINE 0.04%

INACTIVE INGREDIENTS

Water(Aqua), Butylene glycol, Glycerin, Alcohol, Propylene Glycol, 1,2-Hexanediol, PEG/PPG-18/4 Copolymer, Betaine, Phenoxyethanol, Triethanolamine, Carbomer, Allantoin, Ethylhexylglycerin, Glyceryl Acrylate/Acrylic Acid Copolymer, Parfum, PVM/MA Copolymer, Dipropylene Glycol, Thymus Vulgaris (Thyme) Extract, Camellia sinensis Callus Culture extracts, Bambusa Vulgaris Callus Culture Extract, Malva Sylvestris (Mallow) Flower Extract, Leontopodium alpinum extract, Snail Secretion Filtrate, Hydrolyzed Collagen, Sodium Benzoate, Potassium Sorbate, Citric Acid, Caprylyl Glycol, Punica Granatum Fruit Extract, Panax Ginseng Root Extract, Carthamus Tinctorius (Safflower) Flower Extract, Acanthopanax Senticosus (Eleuthero) Root Extract, Solanum Lycopersicum (Tomato) Fruit Extract, Nelumbo Nucifera Seed Extract, Lonicera Japonica (Honeysuckle) Flower Extract, Lilium Tigrinum Extract, Chrysanthemum Indicum Flower Extract, Tropolone, Copper Tripeptide-1, Oligopeptide-1

PURPOSE

Skin Brightening
Anti wrinkle

WARNINGS

For external use only.
Avoid contact with eyes.
Keep out of reach of children.
Discontinue use if signs of irritation appear.

KEEP OUT OF REACH OF CHILDREN

Uses

■ Intensive EGF peptide serum is formulated with EGF, peptide and collagen for brightening and firming.

Directions

■ Can be used daily, AM and PM. Gently massage onto face in circular motions untill absorbed.